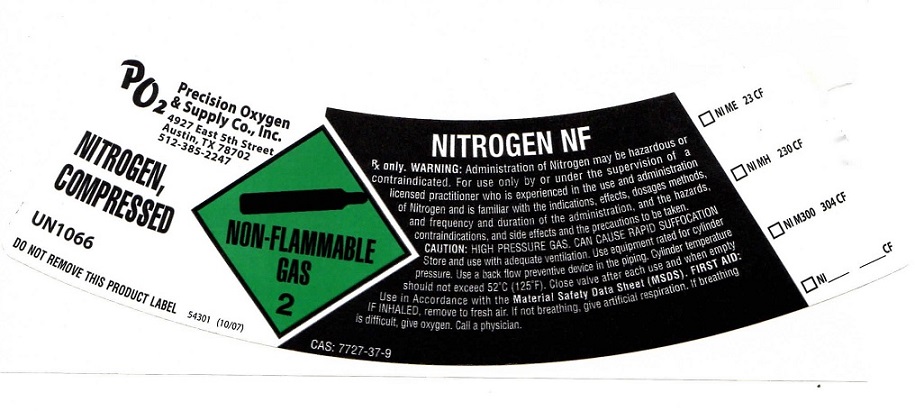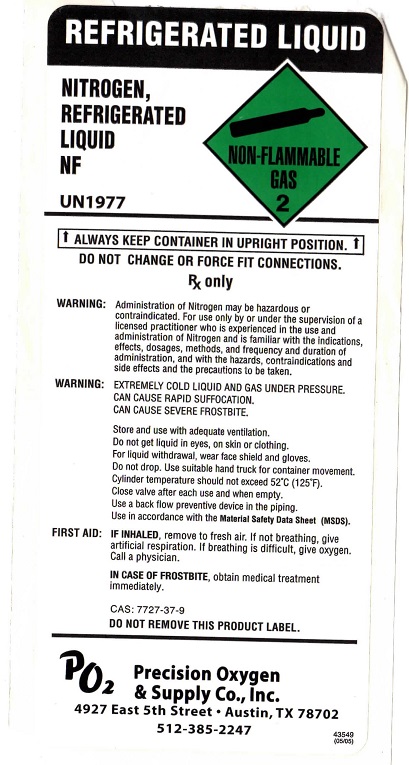 DRUG LABEL: Nitrogen
NDC: 63978-300 | Form: GAS
Manufacturer: Quality Air Products Inc
Category: prescription | Type: HUMAN PRESCRIPTION DRUG LABEL
Date: 20251209

ACTIVE INGREDIENTS: NITROGEN 990 mL/1 L

Nitrogen

PACKAGE LABEL

Precision Oxygen & Supply Co., Inc. 4927 East 5th Street Austin, TX 78702 512-385-2247
NITROGEN, COMPRESSED UN1066 DO NOT REMOVE THIS PRODUCT LABEL.
NON-FLAMMABLE GAS 2 NITROGEN NF
Rx only. WARNING: Administration of Nitrogen may be hazardous or contraindicated. For use only by or under the supervision of a licensed practitioner who is experienced in the use and administration of Nitrogen and is familiar with the indications, effects, dosages, methods, and frequency and duration of administration, and the hazards, contraindications, and side effects and the precautions to be taken. WARNING: CONTAINS HIGH PRESSURE GAS; CAN CAUSE RAPID SUFFOCATION. Store and use with adequate ventilation. Use equipment rated for cylinder pressure. Use a back flow preventive device in the piping. Cylinder temperature should not exceed 52° C (125°F). Close valve after each use and when empty. Use in Accordance with the Material Safety Data Sheet (MSDS). FIRST AID: IF INHALED: Remove to fresh air if not breathing give artificial respiration. If breathing is difficult give oxygen. Call a physician.
CAS: 7727-37-9
NI ME 23 CF NI MH 230 CF NI M300 304 CF NI _____ CF

PACKAGE LABEL

REFRIGERATED LIQUID NITROGEN, REFRIGERATED LIQUID NF UN1977
NON-FLAMMABLE GAS 2
ALWAYS KEEP CONTAINER IN UPRIGHT POSITION. DO NOT CHANGE OR FORCE FIT CONNECTIONS.
Rx ONLY
WARNING: Administration of Nitrogen may be hazardous or contraindicated. For use only by or under the supervision of a licensed practitioner who is experienced in the use and administration of Nitrogen and is familiar with the indications, effects, dosages, methods, and frequency and duration of administration, and with the hazards, contraindications, and side effects and the precautions to be taken.
WARNING: EXTREMELY COLD LIQUID AND GAS UNDER PRESSURE. CAN CAUSE RAPID SUFFOCATION. CAN CAUSE SEVERE FROSTBITE. Store and Use with adequate ventilation. Do not get liquid in eyes, on skin or clothing. For liquid withdrawal, wear face shield and gloves. Do not drop. Use suitable hand truck for container movement. Cylinder temperature should not exceed 52° C (125°F). Close valve after each use and when empty. Use a back flow preventive device in the piping. Use in Accordance with the Material Safety Data Sheet (MSDS).
FIRST AID: IF INHALED, remove to fresh air. If not breathing, give artificial respiration. If breathing is difficult give oxygen. Call a physician. IN CASE OF FROSTBITE, obtain medical treatment immediately.
CAS: 7727-37-9
CONTENTS: LTRS: CU. FT.
DO NOT REMOVE THIS PRODUCT LABEL
Precision Oxygen & Supply Co., Inc. 4927 East 5th Street Austin, TX 78702 512-385-2247